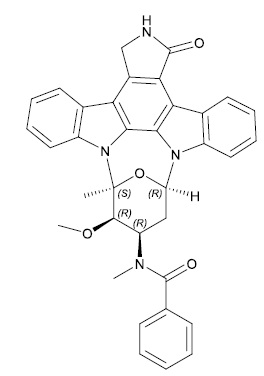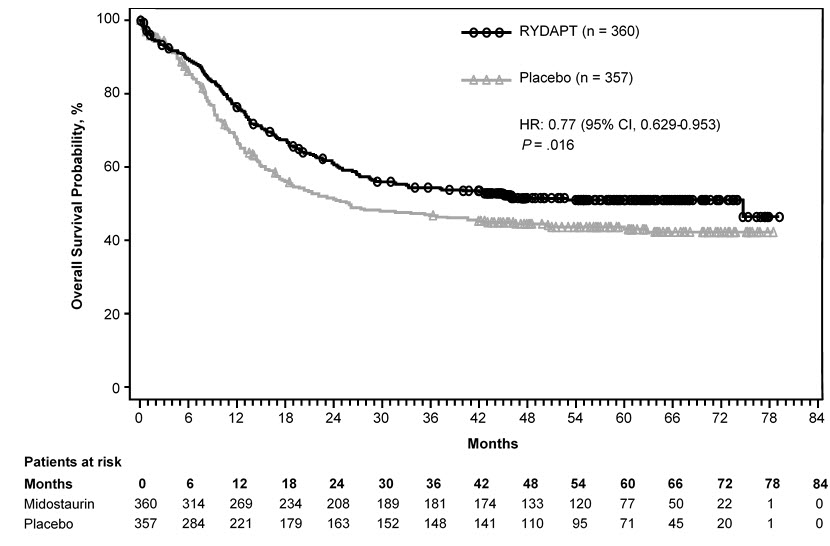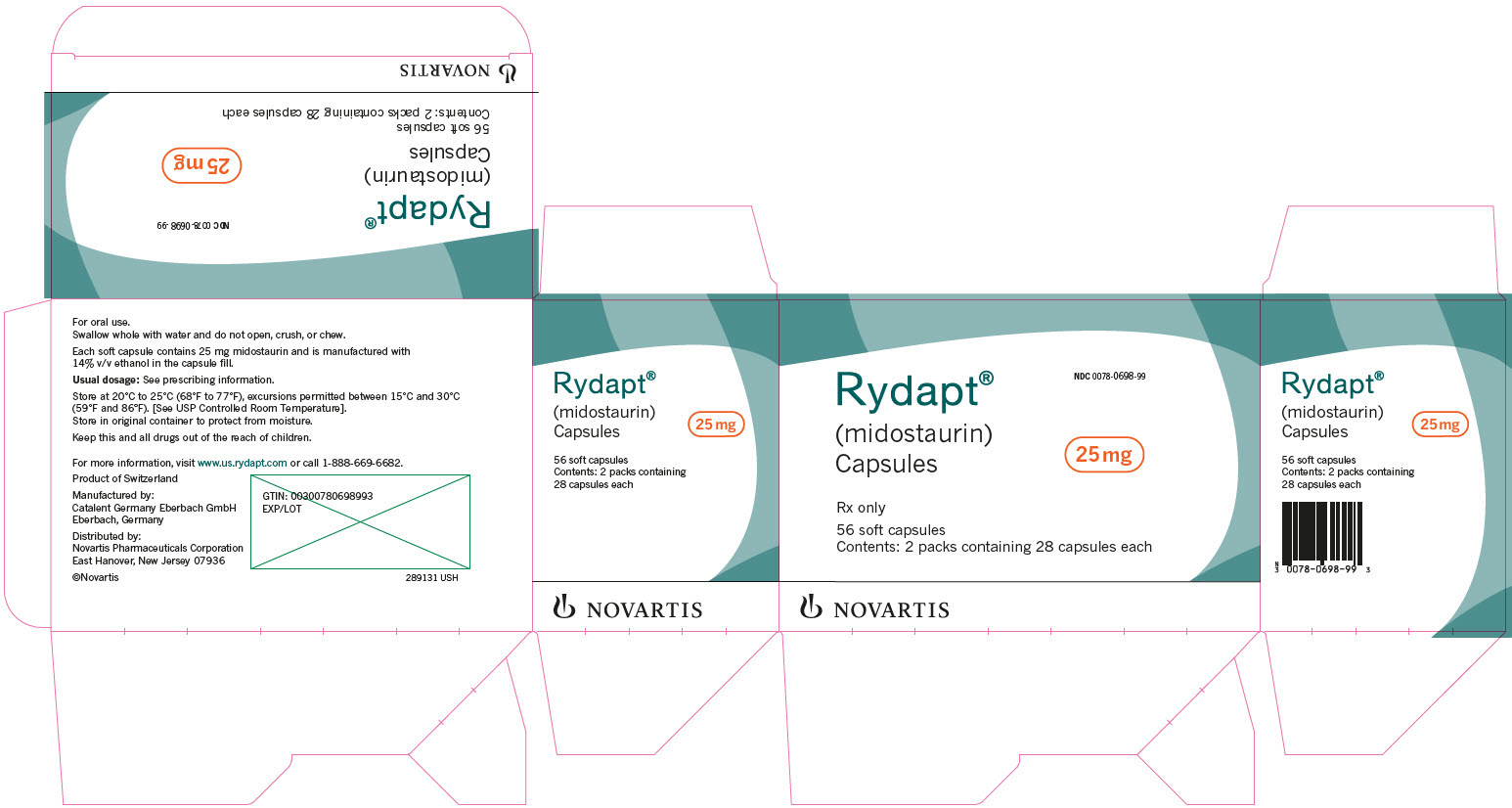 DRUG LABEL: RYDAPT
NDC: 0078-0698 | Form: CAPSULE, LIQUID FILLED
Manufacturer: Novartis Pharmaceuticals Corporation
Category: prescription | Type: HUMAN PRESCRIPTION DRUG LABEL
Date: 20250618

ACTIVE INGREDIENTS: MIDOSTAURIN 25 mg/1 1
INACTIVE INGREDIENTS: POLYOXYL 40 HYDROGENATED CASTOR OIL; GELATIN, UNSPECIFIED; POLYETHYLENE GLYCOL 400; GLYCERIN; ALCOHOL; CORN OIL; TITANIUM DIOXIDE; .ALPHA.-TOCOPHEROL; FERRIC OXIDE YELLOW; FERRIC OXIDE RED; CARMINIC ACID; HYPROMELLOSE 2910 (10000 MPA.S); PROPYLENE GLYCOL; WATER

HIGHLIGHTS OF PRESCRIBING INFORMATION

These highlights do not include all the information needed to use RYDAPT safely and effectively. See full prescribing information for RYDAPT.
RYDAPT® (midostaurin) capsules, for oral use
Initial U.S. Approval: 2017

1 INDICATIONS AND USAGE

RYDAPT is a kinase inhibitor indicated for the treatment of adult patients with:

- Newly diagnosed acute myeloid leukemia (AML) that is FLT3 mutation-positive as detected by an FDA-approved test, in combination with standard cytarabine and daunorubicin induction and cytarabine consolidation. (1.1)
  Limitations of Use: RYDAPT is not indicated as a single-agent induction therapy for the treatment of patients with AML.
- Aggressive systemic mastocytosis (ASM), systemic mastocytosis with associated hematological neoplasm (SM-AHN), or mast cell leukemia (MCL). (1.2)

2 DOSAGE AND ADMINISTRATION

- AML: 50 mg orally twice daily with food. (2.1, 2.2, 2.4)
- ASM, SM-AHN, and MCL: 100 mg orally twice daily with food. (2.3, 2.4)

3 DOSAGE FORMS AND STRENGTHS

Capsules: 25 mg (3)

4 CONTRAINDICATIONS

Hypersensitivity to midostaurin or any of the excipients. (4)

5 WARNINGS AND PRECAUTIONS

- Embryo-Fetal Toxicity: RYDAPT may cause fetal harm when administered to a pregnant woman. Advise of the potential risk to a fetus. (5.1, 8.1)
- Pulmonary Toxicity: Monitor for symptoms of interstitial lung disease or pneumonitis. Discontinue RYDAPT in patients with signs or symptoms of pulmonary toxicity. Fatal cases have occurred. (5.2)

6 ADVERSE REACTIONS

- AML: The most common adverse reactions (≥ 20%) were febrile neutropenia, nausea, mucositis, vomiting, headache, petechiae, musculoskeletal pain, epistaxis, device-related infection, hyperglycemia, electrocardiogram (ECG) QT prolonged, and upper respiratory tract infection. (6.1)
- ASM, SM-AHN, or MCL: The most common adverse reactions (≥ 20%) were nausea, vomiting, diarrhea, edema, musculoskeletal pain, abdominal pain, fatigue, upper respiratory tract infection, constipation, pyrexia, headache, and dyspnea. (6.1)

To report SUSPECTED ADVERSE REACTIONS, contact Novartis Pharmaceuticals Corporation at 1-888-669-6682 and/or at https://report.novartis.com/ or FDA at 1-800-FDA-1088 or www.fda.gov/medwatch.

7 DRUG INTERACTIONS

- Strong CYP3A4 Inhibitors: Strong CYP3A4 inhibitors may increase exposure to midostaurin and its active metabolites. Consider alternative therapies that do not strongly inhibit CYP3A4 or monitor for increased risk of adverse reactions. (7.1)
- Strong CYP3A4 Inducers: Avoid concomitant use as strong CYP3A4 inducers decrease exposure to midostaurin and its active metabolites. (7.1)
- CYP2B6, BCRP, OATP1B1 Substrates: Dose adjustments for coadministered CYP2B6, BCRP, and OATP1B1 substrates may be necessary with RYDAPT. (7.2)

8 USE IN SPECIFIC POPULATIONS

Lactation: Advise females not to breastfeed. (8.2)

FULL PRESCRIBING INFORMATION

1 INDICATIONS AND USAGE

1.1 Acute Myeloid Leukemia

RYDAPT is indicated in combination with standard cytarabine and daunorubicin induction and cytarabine consolidation chemotherapy, for the treatment of adult patients with newly diagnosed acute myeloid leukemia (AML) who are FLT3 mutation-positive, as detected by an FDA approved test [see Dosage and Administration (2.1), Clinical Studies (14.1)].

Limitations of Use

RYDAPT is not indicated as a single-agent induction therapy for the treatment of patients with AML.

1.2 Systemic Mastocytosis

RYDAPT is indicated for the treatment of adult patients with aggressive systemic mastocytosis (ASM), systemic mastocytosis with associated hematological neoplasm (SM-AHN), or mast cell leukemia (MCL).

2 DOSAGE AND ADMINISTRATION

2.1 Patient Selection

Select patients for the treatment of AML with RYDAPT based on the presence of FLT3 mutation positivity [see Clinical Studies (14)]. Information on FDA-approved tests for the detection of FLT3 mutation in AML is available at: http://www.fda.gov/CompanionDiagnostics.

2.2 Recommended Dosage in Acute Myeloid Leukemia

The recommended dose of RYDAPT for patients with AML is 50 mg orally twice daily with food on Days 8 to 21 of each cycle of induction with cytarabine and daunorubicin and on Days 8 to 21 of each cycle of consolidation with high-dose cytarabine. For a description of the experience with single-agent treatment with RYDAPT beyond induction and consolidation [see Clinical Studies (14.1)].

2.3 Recommended Dosage in ASM, SM-AHN, and MCL

The recommended dose of RYDAPT for patients with ASM, SM-AHN, and MCL is 100 mg orally twice daily with food. Continue treatment until disease progression or unacceptable toxicity occurs. Table 1 provides recommendations for dose modifications of RYDAPT in patients with ASM, SM-AHN, and MCL. Monitor patients for toxicity at least weekly for the first 4 weeks, every other week for the next 8 weeks, and monthly thereafter while on treatment.

Table 1: RYDAPT Dose Modifications for Patients with Systemic Mastocytosis
Criteria | RYDAPT Dosing
ANC less than 1 x 10^9/L attributed to RYDAPT in patients without MCL, or ANC less than 0.5 x 10^9/L attributed to RYDAPT in patients with baseline ANC value of 0.5-1.5 x 10^9/L | Interrupt RYDAPT until ANC greater than or equal to 1 x 10^9/L, then resume RYDAPT at 50 mg twice daily, and if tolerated, increase to 100 mg twice daily. Discontinue RYDAPT if low ANC persists for greater than 21 days and is suspected to be related to RYDAPT.
Platelet count less than 50 x 10^9/L attributed to RYDAPT in patients without MCL, or platelet count less than 25 x 10^9/L attributed to RYDAPT in patients with baseline platelet count of 25-75 x 10^9/L | Interrupt RYDAPT until platelet count greater than or equal to 50 x 10^9/L, then resume RYDAPT at 50 mg twice daily, and if tolerated, increase to 100 mg twice daily. Discontinue if low platelet count persists for greater than 21 days and is suspected to be related to RYDAPT.
Hemoglobin less than 8 g/dL attributed to RYDAPT in patients without MCL, or life-threatening anemia attributed to RYDAPT in patients with baseline hemoglobin value of 8 to 10 g/dL | Interrupt RYDAPT until hemoglobin greater than or equal to 8 g/dL, then resume RYDAPT at 50 mg twice daily, and if tolerated, increase to 100 mg twice daily. Discontinue if low hemoglobin persists for greater than 21 days and is suspected to be related to RYDAPT.
Grade 3/4 nausea and/or vomiting despite optimal anti-emetic therapy | Interrupt RYDAPT for 3 days (6 doses), then resume RYDAPT at 50 mg twice daily, and if tolerated, increase to 100 mg twice daily.
Other Grade 3/4 non-hematological toxicities | Interrupt RYDAPT until event has resolved to less than or equal to Grade 2, then resume RYDAPT at 50 mg twice daily, and if tolerated, increase to 100 mg twice daily.
Abbreviations: ANC, absolute neutrophil count; MCL, mast cell leukemia.
National Cancer Institute Common Terminology for Adverse Events (NCI CTCAE) severity: Grade 1 = mild symptoms; 2 = moderate symptoms; 3 = severe symptoms; 4 = life-threatening symptoms.

2.4 Recommended Administration

- Administer prophylactic anti-emetics before treatment with RYDAPT to reduce the risk of nausea and vomiting.
- Administer RYDAPT orally with food, twice daily at approximately 12-hour intervals [see Clinical Pharmacology (12.3)]. Do not open or crush RYDAPT capsules.
- If a dose of RYDAPT is missed or vomited, do not make up the dose; take the next dose at the usual scheduled time.
- Consider interval assessments of QT by electrocardiogram (ECG) if RYDAPT is taken concurrently with medications that can prolong the QT interval.

3 DOSAGE FORMS AND STRENGTHS

25 mg capsules: pale orange oblong soft capsule with red ink imprint ‘PKC NVR’.

4 CONTRAINDICATIONS

RYDAPT is contraindicated in patients with hypersensitivity to midostaurin or to any of the excipients [see Description (11)]. Hypersensitivity reactions have included anaphylactic shock, dyspnea, flushing, chest pain, and angioedema (e.g., swelling of the airways or tongue, with or without respiratory impairment) [see Adverse Reactions (6.1)].

5 WARNINGS AND PRECAUTIONS

5.1 Embryo-Fetal Toxicity

Based on its mechanism of action and findings from animal reproduction studies, RYDAPT may cause fetal harm when administered to pregnant women. In animal studies, midostaurin caused embryo-fetal toxicities, including late embryo-fetal death and reduced fetal birth weight, with delays in fetal growth at doses lower than the recommended human dose. Advise pregnant women of the potential risk to the fetus. Verify the pregnancy status of females of reproductive potential within 7 days prior to initiating RYDAPT therapy. Advise females of reproductive potential to use effective contraception during treatment with RYDAPT and for 4 months after the last dose. Advise males with female partners of reproductive potential to use effective contraception during treatment with RYDAPT and for 4 months after the last dose [see Use in Specific Populations (8.1, 8.3), Clinical Pharmacology (12.1)].

5.2 Pulmonary Toxicity

Cases of interstitial lung disease and pneumonitis, some fatal, have occurred in patients treated with RYDAPT as monotherapy or with chemotherapy.

Monitor patients for pulmonary symptoms. Discontinue RYDAPT in patients who experience signs or symptoms of interstitial lung disease or pneumonitis without an infectious etiology.

5.3 Risk of Prolonged Severe Neutropenia and Thrombocytopenia in Pediatric Patients Treated With Combination Chemotherapy

Prolonged Grade 4 neutropenia and thrombocytopenia occurred in two pediatric patients with AML who received an unapproved formulation of midostaurin in combination with chemotherapy, including anthracyclines, fludarabine, and cytarabine; these two patients were coadministered an azole antifungal (a strong CYP3A4 inhibitor), which may increase midostaurin concentrations and subsequently, the risk of toxicity [see Drug Interactions (7.1), Use in Specific Populations (8.4)]. The safety and effectiveness of RYDAPT in pediatric patients have not been established.

6 ADVERSE REACTIONS

The following serious adverse reactions are described elsewhere in the labeling:

- Pulmonary Toxicity [see Warnings and Precautions (5.2)]

6.1 Clinical Trials Experience

Because clinical trials are conducted under widely varying conditions, adverse reaction rates observed in the clinical trials of a drug cannot be directly compared to rates in the clinical trials of another drug and may not reflect the rates observed in practice.

Acute Myeloid Leukemia

The safety evaluation of RYDAPT (50 mg twice daily with food) in patients with newly diagnosed FLT3 mutated AML is based on a randomized, double-blind, trial of RYDAPT (n = 345) or placebo (n = 335) with chemotherapy [see Clinical Studies (14.1)]. The overall median duration of exposure was 42 days (range, 2 to 576 days) for patients in the RYDAPT plus chemotherapy arm versus 34 days (range, 1 to 465 days) for patients in the placebo plus chemotherapy arm. On the RYDAPT plus chemotherapy arm, 35% of patients completed induction and consolidation therapy, compared to 25% of patients on the placebo plus chemotherapy arm.

The most frequent (incidence greater than or equal to 20%) adverse drug reactions (ADRs) in the RYDAPT plus chemotherapy arm were febrile neutropenia, nausea, mucositis, vomiting, headache, petechiae, musculoskeletal pain, epistaxis, device-related infection, hyperglycemia, ECG QT prolonged, and upper respiratory tract infections. The most frequent Grade 3/4 adverse reactions (incidence ≥ 10%) were febrile neutropenia, device-related infection, and mucositis.

The most frequent serious adverse reaction (≥ 10%) in patients in the RYDAPT plus chemotherapy arm was febrile neutropenia (16%), which occurred at a similar rate in the placebo arm (16%).

Discontinuation due to any adverse reaction occurred in 9% of patients in the RYDAPT arm versus 6% in the placebo arm. The most frequent (> 1%) Grade 3/4 adverse reactions leading to discontinuation in the RYDAPT arm was renal insufficiency (1%).

Excluding deaths due to disease progression, no fatal adverse reactions occurred in the study. Overall, the most frequent non-treatment related cause of death in the RYDAPT plus chemotherapy arm was sepsis (2%) and occurred at a similar rate in the placebo arm (2%).

Table 2 presents the frequency category of adverse reactions reported in the randomized trial in patients with newly diagnosed FLT3 mutated AML. Adverse reactions are listed according to body system. Within each body system, the adverse reactions are ranked by frequency, with the most frequent reactions first. Table 3 presents the key laboratory abnormalities from the same randomized trial in patients with newly diagnosed FLT3 mutated AML.

Table 2: Common Adverse Reactions (≥ 10% Incidence and ≥ 2% More Frequent on the Midostaurin Arm) of Patients with Acute Myeloid Leukemia in Study 1
 | All Grades |  | Grades ≥ 3
Adverse Reaction | RYDAPT + chemo n = 229^1 % | Placebo + chemo n = 226^1 % | RYDAPT + chemo n = 345^1 % | Placebo + chemo n = 335^1 %
Gastrointestinal disorders
Nausea | 83 | 70 | 6 | 10
Mucositisa | 66 | 62 | 11 | 13
Vomiting | 61 | 53 | 3 | 5
Hemorrhoids | 15 | 11 | 1 | 0
Blood and lymphatic system disorders
Febrile neutropenia | 83 | 81 | 84 | 83
Petechiae | 36 | 27 | 1 | 1
Nervous system disorders
Headachea | 46 | 38 | 3 | 3
Musculoskeletal and connective tissue disorders
Musculoskeletal paina | 33 | 31 | 5 | 2
Arthralgia | 14 | 8 | < 1 | < 1
Respiratory, thoracic, and mediastinal disorders
Epistaxis | 28 | 24 | 3 | 1
Infections and infestations
Device-related infection | 24 | 17 | 16 | 10
Upper respiratory tract infectiona | 20 | 15 | 4 | 3
Investigations
Hyperglycemiaa | 20 | 17 | 7 | 6
Electrocardiogram QT prolonged | 20 | 17 | 6 | 5
Activated partial thromboplastin time prolonged | 13 | 8 | 3 | 2
Skin and subcutaneous tissue disorders
Hyperhidrosis | 14 | 8 | 0 | 0
Renal and urinary disorders
Renal insufficiencya | 12 | 9 | 5 | 3
Psychiatric disorders
Insomnia | 12 | 8 | 0 | < 1
^1For trial sites in North America, only Grades 3 and 4 were collected.
aGrouped terms:
• Upper respiratory tract infections: e.g., nasopharyngitis, upper respiratory tract infections, sinusitis.
• Mucositis: e.g., radiation mucositis, stomatitis, laryngeal pain.
• Musculoskeletal pain: e.g., back pain, bone pain, pain in extremity.
• Renal insufficiency: e.g., blood creatinine increased, renal failure, acute kidney injury.
• Hyperglycemia: mainly hyperglycemia.

Other notable adverse reactions occurring in < 10% of patients treated with RYDAPT but at least 2% more frequently than in the placebo group included:

- Infections and infestations: Cellulitisa (7%), fungal infectiona (7%)
- Metabolism and nutrition disorders: Hyperuricemia (8%)
- Nervous system disorders: Tremor (4%)
- Eye disorders: Eyelid edema (3%)
- Cardiac disorders: Hypertensiona (8%), pericardial effusion (4%)
- Respiratory, thoracic, and mediastinal disorders: Pleural effusion (6%)
- Skin and subcutaneous tissue disorders: Dry skin (7%)
- General disorders and administration-site conditions: Thrombosisa (5%)
- Investigations: Weight increased (7%), hypercalcemia (3%)

aGrouped terms:

- Thrombosis: e.g., thrombosis in device, thrombosis.
- Cellulitis: e.g., cellulitis, erysipelas.
- Fungal infection: e.g., bronchopulmonary aspergillosis, pneumonia fungal, splenic infection fungal, hepatic candidiasis.

Other clinically important adverse reactions (All Grades) at ≥ 10% that did not meet criteria for Table 2:

- Respiratory, thoracic, and mediastinal disorders: Pneumonitis (11%)

Table 3: New or Worsening Laboratory Abnormalities (≥ 10% Incidence and ≥ 2% More Frequent on the Midostaurin Arm) Reported in Patients with Acute Myeloid Leukemia on Study 1
Laboratory Abnormality | RYDAPT (50 mg twice daily) N = 345 All Grades % | RYDAPT (50 mg twice daily) N = 345 Grade 3/4 % | Placebo N = 335 All Grades % | Placebo N = 335 Grade 3/4 %
Alanine aminotransferase increased | 71 | 20 | 69 | 16
Hypernatremia | 21 | 1 | 15 | 2
Hypocalcemia | 74 | 7 | 70 | 8

In Study 1, 205 patients (120 in RYDAPT arm and 85 in placebo arm) who remained in remission following completion of consolidation continued to receive either single agent RYDAPT or placebo for a median of 11 months (range, 0.5 to 17 months) with 69 in the RYDAPT arm and 51 in the placebo completing 12 treatment cycles. Common adverse reactions (greater than or equal to 5% difference between the RYDAPT and placebo arms) reported for these patients included nausea (47% vs 18%), hyperglycemia (20% vs 13%), and vomiting (19% vs 5%).

Systemic Mastocytosis

Two single-arm, open-label multicenter trials (Study 2 and Study 3) evaluated the safety of RYDAPT (100 mg twice daily with food) as a single agent in 142 adult patients total with ASM, SM-AHN, or MCL. The median age was 63 (range, 24 to 82), 63% had an Eastern Cooperative Oncology Group (ECOG) performance status of 0 or 1, and 75% had no hepatic impairment (bilirubin and AST ≤ upper limit of normal (ULN)] at baseline. The median duration of exposure to RYDAPT was 11.4 months (range, 0 to 81 months), with 34% treated for ≥ 24 months.

The most frequent adverse reactions (≥ 20%), excluding laboratory terms, were nausea, vomiting, diarrhea, edema, musculoskeletal pain, abdominal pain, fatigue, upper respiratory tract infection, constipation, pyrexia, headache, and dyspnea (Table 4). Grade ≥ 3 adverse reactions reported in ≥ 5%, excluding laboratory terms, were fatigue, sepsis, gastrointestinal hemorrhage, pneumonia, diarrhea, febrile neutropenia, edema, dyspnea, nausea, vomiting, abdominal pain, and renal insufficiency (Table 4).

Adverse reactions led to dose modifications (interruption or reduction) in 56% of patients. Among these, the most frequent adverse reactions (> 5%) were gastrointestinal symptoms, QT prolongation, neutropenia, pyrexia, thrombocytopenia, gastrointestinal hemorrhage, lipase increase, and fatigue. The median time to first dose modification for toxicity was 1.6 months, with 75% of dose modifications first occurring within 5 months of starting treatment.

Treatment discontinuation due to adverse reactions occurred in 21% of patients. The most frequent adverse reactions causing treatment discontinuation included infection, nausea or vomiting, QT prolongation, and gastrointestinal hemorrhage.

Serious adverse reactions were reported in 68% of patients, most commonly (≥ 20%) due to infections and gastrointestinal disorders.

On-treatment deaths unrelated to the underlying malignancy occurred in 16 patients (11%), most commonly from infection (sepsis or pneumonia), followed by cardiac events. Of the on-treatment deaths from disease progression, 4 were also attributable to infection.

Table 4 summarizes the adverse reactions reported in ≥ 10% of the patients with advanced SM.

Table 4: Adverse Reactions Reported in ≥ 10% of Patients with Advanced Systemic Mastocytosis (Study 2 and Study 3)
 | RYDAPT (100 mg twice daily) N = 142
Adverse Reactiona | All Grades % | Grade ≥ 3 %
Gastrointestinal disorders
Nausea | 82 | 6
Vomiting | 68 | 6
Diarrheaa | 54 | 8
Abdominal paina | 34 | 6
Constipation | 29 | < 1
Gastrointestinal hemorrhagea | 14 | 9
General disorders and administration-site conditions
Edemaa | 40 | 7
Fatiguea | 34 | 9
Pyrexia | 27 | 4
Infections and infestations
Upper respiratory tract infectiona | 30 | 1
Urinary tract infectiona | 16 | 3
Pneumoniaa | 10 | 8
Herpesvirus infectiona | 10 | 1
Musculoskeletal and connective tissue disorders
Musculoskeletal paina | 35 | 4
Arthralgia | 19 | 2
Nervous system disorders
Headachea | 26 | 1
Dizziness | 13 | 0
Respiratory, thoracic, and mediastinal disorders
Dyspneaa | 23 | 7
Cougha | 18 | < 1
Pleural effusion | 13 | 4
Epistaxis | 12 | 3
Skin and subcutaneous disorders
Rasha | 14 | 3
Investigations
QT prolonged | 11 | < 1
Psychiatric disorders
Insomnia | 11 | 0
Renal disorders
Renal insufficiencya | 11 | 5
Toxicity was graded per National Cancer Institute Common Terminology Criteria for Adverse Events (NCI CTCAE) version 3.
Represents adverse reactions, excluding laboratory terms, occurring up to 28 days after last midostaurin dose, regardless of baseline grade.
a Grouped terms:
- Upper respiratory tract infection: e.g., nasopharyngitis, upper respiratory tract infections.
- Urinary tract infection: e.g., urinary tract infection, cystitis.
- Pneumonia: e.g., pneumonia, lung infection.
- Herpesvirus infection: e.g., oral herpes, herpes zoster.
- Headache: e.g., headache, sinus headache.
- Dyspnea: e.g., dyspnea, bronchospasm, respiratory failure.
- Cough: e.g., cough, productive cough.
- Diarrhea: e.g., diarrhea, gastroenteritis, colitis.
- Abdominal pain: e.g., abdominal pain, abdominal pain upper.
- Gastrointestinal hemorrhage: e.g., gastrointestinal hemorrhage, hemorrhoidal hemorrhage, duodenal ulcer hemorrhage.
- Fatigue: e.g., fatigue, asthenia.
- Rash: e.g., rash, rash maculo-papular, erythema multiforme.
- Musculoskeletal pain: e.g., back pain, musculoskeletal pain, pain in extremity.
- Renal insufficiency: e.g., blood creatinine increased, renal failure, acute kidney injury.
- Edema: e.g., edema, edema peripheral.

Gastrointestinal Toxicities Leading to Treatment Modification: In patients with advanced SM, the median time to onset of nausea was 9 days, with 75% of cases beginning within the first 3 months. The median time to onset of vomiting was 1 month.

Other clinically significant adverse reactions occurring in ≤ 10% of patients included:

Infections and infestations: Sepsis (9%)a, bronchitis (6%), cellulitis or erysipelas (5%)

Blood and lymphatic system disorders: Febrile neutropenia (8%)

Cardiac disorders: Cardiac failure (6%), myocardial infarction, or ischemia (4%)a

Immune system disorders: Hypersensitivity (4%)a

Nervous system disorders: Disturbance in attention (7%), tremor (6%), mental status changes (4%)

Ear and labyrinth disorders: Vertigo (5%)

Vascular disorders: Hypotension (9%), hematoma (6%)

Respiratory, thoracic, and mediastinal disorders: Oropharyngeal pain (4%), pulmonary edema (3%)a, interstitial lung disease (1%), pneumonitis (<1%)

Gastrointestinal disorders: Dyspepsia (6%), gastritis (3%)a

General disorders and administration site conditions: Chills (5%)

Investigations: Weight increased (6%)

Injury, poisoning, and procedural complications: Contusion (6%)

a Grouped terms:

- Sepsis: e.g., sepsis, staphylococcal/Enterobacter/Escherichia sepsis
- Hypersensitivity: includes one report of anaphylactic shock
- Myocardial infarction or ischemia: e.g., myocardial infarction and acute myocardial infarction, angina pectoris
- Gastritis: gastritis, gastritis erosive, gastritis hemorrhagic
- Pulmonary edema: pulmonary edema, pulmonary congestion

Table 5 summarizes new or worsening laboratory abnormalities. Common (≥ 10%) Grade 3 or higher non-hematologic laboratory abnormalities were hyperglycemia (non-fasting), lipase increase, and hyperuricemia. The most common (≥ 20%) Grade 3 or higher hematologic laboratory abnormalities were lymphopenia, anemia, thrombocytopenia, and neutropenia. Grade 4 hematologic abnormalities occurring in ≥ 5% were thrombocytopenia (13%), neutropenia (8%), anemia (6%), and lymphopenia (6%).

Table 5: Most Common (≥ 20%) New or Worsening Laboratory Abnormalities Reported in Patients with Advanced Systemic Mastocytosis (Study 2 and Study 3)
 | RYDAPT (100 mg twice daily) N = 142
Test | All Grades % | Grade ≥ 3 %
Hematology
Lymphopenia | 66 | 42
Leukopenia | 61 | 19
Anemia | 60 | 38
Thrombocytopenia | 50 | 27
Neutropenia | 49 | 22
Chemistry
Hyperglycemiaa | 80 | 18
Alk phos increase | 39 | 9
Hypocalcemia | 39 | 2
Lipase increase | 37 | 18
Hyperuricemia | 37 | 11
GGT increaseb | 35 | 9
Hyponatremia | 34 | 5
AST increase | 32 | 3
ALT increase | 31 | 4
Hyperbilirubinemia | 29 | 4
Hypoalbuminemia | 27 | 1
Hypokalemia | 25 | 6
Creatinine increase | 25 | < 1
Hyperkalemia | 23 | 4
Hypophosphatemia | 22 | 1
Amylase increase | 20 | 7
Hypomagnesemia | 20 | 0
Abbreviations: Alk phos, alkaline phosphatase; ALT, alanine aminotransferase; AST, aspartate aminotransferase; GGT, gamma glutamyltransferase.
Includes abnormalities occurring up to 28 days after last midostaurin dose, if new or worsened from baseline or if baseline was unknown.
aNon-fasting.
bAmong 116 evaluable patients.

6.2 Postmarketing Experience

The following adverse drug reactions have been derived from postmarketing experience with RYDAPT via spontaneous case reports and literature cases. Because these reactions are reported voluntarily from a population of uncertain size, it is not always possible to reliably estimate their frequency or establish a causal relationship to drug exposure.

- Respiratory, thoracic, and mediastinal disorders: Interstitial lung disease
- Skin and subcutaneous tissue disorders: Acute febrile neutrophilic dermatosis (Sweet syndrome)

7 DRUG INTERACTIONS

7.1 Effect of Other Drugs on RYDAPT

Table 6 lists the potential effects of the coadministration of strong CYP3A modulators on RYDAPT.

Table 6: Drug Interactions with RYDAPT That Affect Midostaurin
Strong CYP3A Inhibitors
Clinical Impact | - Coadministration of RYDAPT with strong CYP3A inhibitors may increase midostaurin concentrations. The increase in midostaurin concentrations may be pronounced if strong CYP3A inhibitors are administered during the first week of RYDAPT administration [see Clinical Pharmacology (12.3)]. - Increased midostaurin concentrations may increase the risk of toxicity.
Prevention or Management | - Consider alternative therapies that do not strongly inhibit CYP3A activity. - Alternatively, with coadministration of RYDAPT and strong CYP3A inhibitors, monitor patients for increased risk of adverse reactions, especially during the first week of consecutive RYDAPT administration in advanced SM population, and during first week of RYDAPT administration in each cycle of chemotherapy in AML population.
Examples | Boceprevir, clarithromycin, cobicistat, conivaptan, danoprevir and ritonavir, diltiazem, elvitegravir and ritonavir, grapefruit juicea, idelalisib, indinavir and ritonavir, itraconazole, ketoconazole, lopinavir and ritonavir, nefazodone, nelfinavir, paritaprevir and ritonavir and (ombitasvir and/or dasabuvir), posaconazole, ritonavir, saquinavir and ritonavir, tipranavir and ritonavir, troleandomycin, voriconazole
Strong CYP3A Inducers
Clinical Impact | - Coadministration of RYDAPT with strong CYP3A inducers may decrease midostaurin concentrations [see Clinical Pharmacology (12.3)]. - Decreased midostaurin concentrations may reduce efficacy.
Prevention or Management | Avoid coadministration of RYDAPT with strong CYP3A4 inducers.
Examples | Carbamazepine, enzalutamide, mitotane, phenytoin, rifampin, St. John’s wortb
aThe effect of grapefruit juice varies widely among brands and is concentration-, dose-, and preparation-dependent. Studies have shown that it can be classified as a “strong CYP3A inhibitor” when a certain preparation was used (e.g., high dose, double strength) or as a “moderate CYP3A inhibitor” when another preparation was used (e.g., low dose, single strength).
bThe induction potency of St. John’s wort may vary widely based on preparation.

7.2 Effect of RYDAPT on Other Drugs

CYP2B6 Substrates

RYDAPT decreased the systemic exposure of a sensitive CYP2B6 substrate [see Clinical Pharmacology (12.3)]. Dose adjustments for the coadministered CYP2B6 substrate may be necessary with RYDAPT.

Substrates of Transporters

Coadministration of RYDAPT increased the exposure of a breast cancer resistance protein (BCRP) and organic anion transporter polypeptide (OATP)1B1 substrate [see Clinical Pharmacology (12.3)]. Dose adjustments for the coadministered BCRP or OATP1B1 substrates may be necessary with RYDAPT.

8 USE IN SPECIFIC POPULATIONS

8.1 Pregnancy

Pregnancy Exposure Registry

There is a pregnancy exposure registry that monitors pregnancy outcomes in women exposed to RYDAPT during pregnancy. Females who may have been exposed to RYDAPT during pregnancy directly or through a male partner receiving RYDAPT therapy should contact the Novartis Pharmaceuticals Corporation at 1-888-669-6682 and/or at https://report.novartis.com/.

Risk Summary

Based on mechanism of action and findings in animal reproduction studies, RYDAPT may cause fetal harm when administered to a pregnant woman [see Clinical Pharmacology (12.1)]. There are no available data on RYDAPT use in pregnant women to inform a drug-associated risk of major birth defects and miscarriage. In animal reproduction studies, oral administration of midostaurin to pregnant rats and rabbits during organogenesis caused embryo-fetal toxicities, including late embryo-fetal death and reduced fetal birth weight, with delays in fetal growth at doses lower than the recommended human dose (see Data). Advise pregnant women of the potential risk to a fetus.

The background risk of major birth defects and miscarriage for the indicated population are unknown. Adverse outcomes in pregnancy occur regardless of the health of the mother or the use of medications. In the U.S. general population, the estimated background risk of major birth defects and miscarriage in clinically recognized pregnancies is 2% to 4% and 15% to 20%, respectively.

Data

Animal Data

When midostaurin was administered to female rats prior to mating and through the first week of pregnancy at a dose of 60 mg/kg/day [approximately 0.1 times the human exposure at the recommended dose based on area under the curve (AUC)], there were increases in pre- and post-implantation loss, including total litter loss, resulting in a reduction in the number of live embryos.

During organogenesis, midostaurin administered at oral doses greater than or equal to 3 mg/kg/day (approximately 0.004 times the human exposure at the recommended dose by AUC) to pregnant female rats caused late embryo-fetal death. Dilated lateral brain ventricles were observed in offspring of rats given doses greater than or equal to 3 mg/kg/day. Extra rib and reduced fetal birth weight with effects on fetal growth (severe renal pelvic cavitation and widened anterior fontanelle) were observed in the absence of maternal toxicity at the highest dose of 30 mg/kg/day (approximately 0.05 times the human exposure at the recommended dose by AUC). Midostaurin administered orally to pregnant rabbits during organogenesis led to maternal toxicity with spontaneous abortions and some delay in fetal growth (reduced fetal birth weight) at doses greater than or equal to 10 mg/kg/day (approximately 0.01 times the human exposure at the recommended dose by AUC).

In an oral pre- and postnatal development study in the rat, adverse effects upon maternal performance included dams with signs of dystocia and a lower live litter size at 30 mg/kg/day (approximately 0.05 times the human exposure at the recommended dose by AUC). For the F1 offspring, lower body weights, accelerated complete eye opening and delayed auricular startle ontogeny were noted at 30 mg/kg/day.

8.2 Lactation

Risk Summary

There are no data on the presence of midostaurin or its active metabolites in human milk, the effect on the breastfed infant, or the effect on milk production. Orally administered midostaurin and its active metabolites pass into the milk of lactating rats within 1 hour of a 30 mg/kg/day dose, with approximately 5 times more in the milk of lactating rats compared to plasma. Because of the potential for serious adverse reactions in breastfed infants from RYDAPT, advise women not to breastfeed during treatment with RYDAPT and for 4 months after the last dose.

8.3 Females and Males of Reproductive Potential

RYDAPT may cause fetal harm when administered to a pregnant woman [see Use in Specific Populations (8.1)].

Pregnancy Testing

Pregnancy testing is recommended for females of reproductive potential within seven days prior to initiating RYDAPT.

Contraception

Females

Advise females of reproductive potential to use effective contraception during treatment with RYDAPT and for 4 months after the last dose.

Males

Advise males with female partners of reproductive potential to use effective contraception during RYDAPT treatment and for 4 months after stopping treatment with RYDAPT [see Nonclinical Toxicology (13.1)].

Infertility

Based on findings in animals, RYDAPT may impair fertility in females and males of reproductive potential. It is not known whether these effects on fertility are reversible [see Nonclinical Toxicology (13.1)].

8.4 Pediatric Use

Safety and effectiveness of RYDAPT have not been established in pediatric patients.

The safety and effectiveness of an unapproved midostaurin formulation was investigated, but not established in two open-label studies: a study in 22 pediatric patients aged 6 months to 17 years who received midostaurin as a single agent for relapsed or refractory leukemia [NCT00866281] and a study in 4 patients aged 8 to 14 years who received midostaurin in combination with chemotherapy for newly diagnosed FLT3-mutated AML [NCT03591510]. Prolonged Grade 4 neutropenia and thrombocytopenia occurred in 2 of the 4 pediatric patients with AML who received midostaurin in combination with chemotherapy, including anthracyclines, fludarabine, and cytarabine [see Warnings and Precautions (5.3)]. Grade 4 thrombocytopenia lasted for 44 days in one patient and Grade 4 thrombocytopenia and Grade 4 neutropenia lasted for 51 days and 46 days, respectively, in the other patient. These two patients were coadministered an azole antifungal (a strong CYP3A4 inhibitor), which may increase midostaurin concentrations and subsequently, the risk of toxicity [see Drug Interactions (7.1)].

8.5 Geriatric Use

Of the 142 patients with advanced SM in clinical studies of RYDAPT, 64 (45%) were aged 65 and over, and 16 (11%) were aged 75 years and over. No overall differences in safety or response rate were observed between the subjects aged 65 and over compared with younger subjects. Greater sensitivity of older individuals cannot be ruled out.

Clinical studies in AML with RYDAPT did not include sufficient numbers of subjects aged 65 and over to determine whether they respond differently from younger subjects.

In general, administration for elderly patients should be cautious, based on patient’s eligibility for concomitant chemotherapy and reflecting the greater frequency of concomitant disease or other drug therapy.

11 DESCRIPTION

Midostaurin is a kinase inhibitor for oral use. The molecular formula for midostaurin is C35H30N4O4. The molecular weight is 570.65 g/mol. The chemical name of midostaurin is Benzamide, N-[(9S,10R,11R,13R)-2,3,10,11,12,13-hexahydro-10-methoxy-9-methyl-1-oxo-9,13-epoxy-1H,9H-diindolo[1,2,3-gh:3′,2′,1′-lm]pyrrolo[3,4-j][1,7]benzodiazonin-11-yl]-N-methyl-. The chemical structure of midostaurin is shown below:

RYDAPT is supplied as a soft capsule containing 25 mg of midostaurin. The capsule contains carmine, corn oil mono-di-triglycerides, dehydrated alcohol, ferric oxide red, ferric oxide yellow, gelatin, glycerin 85%, hypromellose 2910, polyethylene glycol 400, polyoxyl 40 hydrogenated castor oil, propylene glycol, purified water, titanium dioxide, and vitamin E.

12 CLINICAL PHARMACOLOGY

12.1 Mechanism of Action

Midostaurin is a small molecule that inhibits multiple receptor tyrosine kinases. In vitro biochemical or cellular assays have shown that midostaurin or its major human active metabolites CGP62221 and CGP52421 inhibit the activity of wild type FLT3, FLT3 mutant kinases (ITD and TKD), KIT (wild type and D816V mutant), PDGFRα/β, as well as members of the serine/threonine kinase PKC (protein kinase C) family.

Midostaurin demonstrated the ability to inhibit FLT3 receptor signaling and cell proliferation, and it induced apoptosis in leukemic cells expressing ITD and TKD mutant FLT3 receptors or overexpressing wild type FLT3 and PDGF receptors. Midostaurin also demonstrated the ability to inhibit KIT signaling, cell proliferation and histamine release and induce apoptosis in mast cells.

12.2 Pharmacodynamics

Cardiac Electrophysiology

The effect of RYDAPT (75 mg twice daily for 3 days) on the QTc interval was evaluated in a randomized, placebo and moxifloxacin controlled, multiple-dose, blinded, parallel study. There was no clinically significant prolongation of QTc interval or relationship between changes in QTc and concentrations for midostaurin and its active metabolites (CGP62221 and CGP52421). The study duration was not long enough to estimate the effects of the metabolite CGP52421 on the QT/QTc interval.

In pooled clinical studies in patients with advanced SM, 4.7% patients had a post-baseline QTcF > 480 ms, no patients had a QTcF > 500 ms, and 6.3% patients had a QTcF > 60 ms compared to baseline.

In a randomized placebo-controlled study in patients with AML, the proportion of patients with QTc prolongation was higher in patients randomized to midostaurin as compared to placebo (QTcF > 480 ms: 10.1% vs 5.7%; QTcF > 500 ms: 6.2% vs 2.6%; QTcF > 60 ms change from baseline: 18.4% vs 10.7%).

12.3 Pharmacokinetics

Midostaurin exhibits time-dependent pharmacokinetics with an initial increase in minimum concentrations (Cmin) that reach the highest Cmin concentrations during the first week followed by a decline to a steady-state after approximately 28 days. The pharmacokinetics of the CGP62221 showed a similar trend. The plasma concentrations of CGP52421 continued to increase after one month of treatment.

The highest Cmin and steady-state of midostaurin, CGP62221, and CGP52421 were similar when RYDAPT was administered with food at a dose of 50 mg twice daily or 100 mg twice daily.

Absorption

The time to maximal concentrations (Tmax) occurred between 1 to 3 hours post dose in the fasted state.

Effect of Food

Midostaurin exposure, represented by AUC over time to infinity (AUCinf), increased 1.2-fold when RYDAPT was coadministered with a standard meal (457 calories, 50 g fat, 21 g proteins, and 18 g carbohydrates) and 1.6-fold when coadministered with a high-fat meal (1007 calories, 66 g fat, 32 g proteins, and 64 g carbohydrates) compared to when RYDAPT was administered in a fasted state. Midostaurin maximum concentrations (Cmax) were reduced by 20% with a standard meal and by 27% with a high-fat meal compared to a fasted state. Tmax was delayed when RYDAPT was administered with a standard meal or a high-fat meal (median Tmax = 2.5 hrs to 3 hrs) [see Dosage and Administration (2.5)].

Distribution

Midostaurin has an estimated geometric mean volume of distribution (% coefficient of variation) of 95.2 L (31%). Midostaurin and its metabolites are distributed mainly in plasma in vitro. Midostaurin, CGP62221, and CGP52421 are greater than 99.8% bound to plasma protein in vitro. Midostaurin is mainly bound to α1-acid glycoprotein in vitro.

Elimination

The geometric mean terminal half-life (% coefficient of variation) is 19 hours (39%) for midostaurin, 32 hours (31%) for CGP62221 and 482 hours (25%) for CGP52421.

Metabolism

Midostaurin is primarily metabolized by CYP3A4. CGP62221 and CGP52421 (mean ± standard deviation) account for 28 ± 2.7% and 38 ± 6.6% respectively of the total circulating radioactivity.

Excretion

Fecal excretion accounted for 95% of the recovered dose with 91% of the recovered dose excreted as metabolites and 4% of the recovered dose as unchanged midostaurin. Only 5% of the recovered dose was found in urine.

Specific Populations

Age (20 to 94 years), sex, race, mild (total bilirubin greater than 1.0 to 1.5 times the ULN or aspartate aminotransferase (AST) greater than the ULN) or moderate (total bilirubin 1.5 to 3.0 times the ULN and any value for AST) hepatic impairment, and renal impairment (creatinine clearance (CLCr) ≥ 30 mL/min) did not have clinically meaningful effects on the pharmacokinetics of midostaurin, CGP62221, or CGP52421. The pharmacokinetics of midostaurin in patients with baseline severe hepatic impairment (total bilirubin greater than 3.0 times the ULN and any value for AST) or severe renal impairment (CLCr 15 to 29 mL/min) is unknown.

Drug Interaction Studies

Clinical Studies and Model-Informed Approaches

Effect of Strong CYP3A4 Inhibitors on Midostaurin

Coadministration of ketoconazole (a strong CYP3A4 inhibitor) with a single dose of RYDAPT (50 mg) increased AUCinf of midostaurin by 10.4-fold and CGP62221 by 3.5-fold and area under the curve over time to last measurable concentrations (AUC0-t) of CGP52421 by 1.2-fold compared to a single RYDAPT dose coadministered with placebo [see Drug Interactions (7.1)].

Coadministration of itraconazole (a strong CYP3A4 inhibitor) with multiple doses of RYDAPT (100 mg twice daily on Days 1 to 2 and 50 mg twice daily on Days 3 to 28) increased Day 28 Cmin concentrations of midostaurin by 2.1-fold, CGP62221 by 1.2-fold, and CGP52421 by 1.3-fold compared to the respective Day 21 Cmin concentrations with RYDAPT alone [see Drug Interactions (7.1)].

Effect of Strong CYP3A4 Inducers on Midostaurin

Coadministration of rifampicin (a strong CYP3A4 inducer) with a single dose of RYDAPT (50 mg) decreased AUCinf of midostaurin by 96% and CGP62221 by 92% and AUC0-t of CGP52421 by 59% [see Drug Interactions (7.1)].

Effect of Midostaurin on CYP2B6 Substrates

Coadministration of multiple doses of RYDAPT (50 mg twice daily) at steady-state with a single dose of bupropion (a sensitive CYP2B6 substrate) decreased the AUCinf of bupropion by 48% and hydroxybupropion by 65% [see Drug Interactions (7.2)].

Effect of Midostaurin on CYP3A, CYP2C8, CYP2D6 Substrates

Coadministration of multiple doses of RYDAPT (50 mg twice daily) at steady-state with single doses of midazolam (a sensitive CYP3A substrate) or pioglitazone (a moderate sensitive CYP2C8 substrate) did not affect AUCinf of midazolam or pioglitazone. However, the effect of multiple doses of RYDAPT on sensitive substrates of CYP3A and CYP2C8 during the first week, when midostaurin trough concentrations are highest, is unknown.

Coadministration of a single dose of RYDAPT (100 mg) with a single dose of dextromethorphan (a sensitive CYP2D6 substrate) did not affect the AUCinf of dextromethorphan. The effect of multiple doses of RYDAPT on dextromethorphan is unknown.

Coadministration of multiple doses of RYDAPT (50 mg twice daily) at steady-state with a single dose of a hormonal contraceptive containing ethinyl estradiol and levonorgestrel (CYP3A4 substrates) increased the area under the curve over time to the last measurable concentration (AUClast) of ethinyl estradiol by 10% and levonorgestrel by 42%. However, the effect of multiple doses of RYDAPT on ethinyl estradiol and levonorgestrel during the first week, when midostaurin trough concentrations are highest, is unknown.

Effect of Midostaurin on P-gp, BCRP, and OATP1B1 Substrates

Coadministration of a single dose of RYDAPT (100 mg) with a single dose of rosuvastatin (BCRP and OATP1B1 substrate) increased the AUClast of rosuvastatin by 48%. RYDAPT 50 mg twice daily at steady state is predicted to increase the AUC of an OATP1B1 substrate up to 2-fold, with unknown effect on a BCRP substrate [see Drug Interactions (7.2)].

Coadministration of a single dose of RYDAPT (100 mg) with a single dose of digoxin (sensitive P-gp substrate) did not affect the AUCinf of digoxin. The effect of multiple doses of RYDAPT on digoxin is unknown.

In Vitro Studies

Effect of Midostaurin on CYP Enzymes

Midostaurin inhibits CYP1A2 and CYP2E1; CGP62221 inhibits CYP1A2 in vitro. Midostaurin, CGP52421, and CGP62221 induce CYP1A2 in vitro.

13 NONCLINICAL TOXICOLOGY

13.1 Carcinogenesis, Mutagenesis, Impairment of Fertility

Carcinogenicity studies have not been performed with midostaurin.

Midostaurin was not mutagenic in vitro in the bacterial reverse mutation assay (Ames test) or in Chinese hamster V97 cells. Midostaurin increased the frequency of polyploidy cells in an in vitro chromosomal aberrations assay in Chinese hamster ovary cells, but was not clastogenic in an in vivo rat bone marrow micronucleus assay when tested to the maximum tolerated dose (MTD) of 200 mg/kg (1,200 mg/m^2). This dose was approximately 20-fold the recommended human dose, based on body surface area.

Reproductive toxicity was observed in a fertility study, in male and female rats given oral doses of midostaurin at 10, 30 and 60 mg/kg/day (approximately 0.01, 0.05, and 0.1 times, respectively, the AUC at the recommended human dose). In males, testicular degeneration and atrophy was observed at doses greater than or equal to 10 mg/kg/day and reduced sperm count and motility, and a decrease in reproductive organ weights were observed at 60 mg/kg/day. In females, increased resorptions, decreased pregnancy rate, and decreased number of implants and live embryos were observed at 60 mg/kg/day. In a 3-month toxicology study in dogs, there was inhibition of spermatogenesis at doses greater than or equal to 3 mg/kg/day (approximately 0.01 times the exposure at the recommended human dose).

14 CLINICAL STUDIES

14.1 Acute Myeloid Leukemia

Study 1

RYDAPT in combination with chemotherapy was investigated in a randomized, double-blind placebo-controlled trial of 717 patients with newly-diagnosed FLT3-mutated AML. In this study, FLT3 mutation status was determined prospectively with a clinical trial assay and verified retrospectively using the companion diagnostic LeukoStrat® CDx FLT3 Mutation Assay, which is an FDA-approved test for selection of patients with AML for RYDAPT treatment. Patients were stratified by FLT3 mutation status: TKD, ITD with allelic ratio less than 0.7, and ITD with allelic ratio greater than or equal to 0.7. Patients with acute promyelocytic leukemia or therapy-related AML were not eligible. Patients were randomized (1:1) to receive RYDAPT 50 mg twice daily (n = 360) or placebo (n = 357) with food on Days 8 to 21 in combination with daunorubicin (60 mg/m^2 daily on Days 1 to 3) /cytarabine (200 mg/m^2 daily on Days 1 to 7) for up to two cycles of induction and high dose cytarabine (3 g/m^2 every 12 hours on Days 1, 3, and 5) for up to four cycles of consolidation, followed by continuous RYDAPT or placebo treatment according to initial assignment for up to 12 additional 28-day cycles. There was no re-randomization at the start of post consolidation therapy. Patients who proceeded to hematopoietic stem cell transplantation (SCT) stopped receiving study treatment.

The randomized patients had a median age of 47 years (range, 18 to 60 years), 44% were male, and 88% had a performance status of 0-1. AML was de novo onset in 95%. The percentage of patients with FLT3-ITD allelic ratio < 0.7, FLT3-ITD allelic ratio ≥ 0.7, and FLT3-TKD mutations were identical (per randomized FLT3 stratum) on both arms (48%, 30%, and 23%, respectively). Of the 563 patients with NPM1 testing, 58% had an NPM1 mutation. The two treatment groups were generally balanced with respect to the baseline demographics and disease characteristics, except that the placebo arm had a higher percentage of females (59%) than in the midostaurin arm (52%). NPM1 mutations were identified in 55% of patients tested on the midostaurin arm and 60% of patients tested on the placebo arm.

A second course of induction was administered to 25% of the patients, 62% initiated at least one cycle of consolidation, 29% initiated maintenance, and 17% completed all 12 planned cycles of maintenance; 21% of the patients underwent SCT in first CR. The overall rate of SCT (induction failure, first CR or salvage after relapse) was 59% (214/360) of patients in the RYDAPT plus standard chemotherapy arm versus 55% (197/357) in the placebo plus standard chemotherapy arm. All patients were followed for survival.

Efficacy was established on the basis of overall survival (OS), measured from the date of randomization until death by any cause. The primary analysis was conducted after a minimum follow-up of approximately 3.5 years after the randomization of the last patient. RYDAPT plus standard chemotherapy was superior to placebo plus standard chemotherapy in OS [HR 0.77; 95% confidence interval (CI) 0.63, 0.95; 2-sided p = 0.016] (Figure 1). Because survival curves plateaued before reaching the median, median survival could not be reliably estimated.

Figure 1: Kaplan-Meier Curve for Overall Survival in Study 1

The analysis of event-free survival (EFS), defined as a failure to obtain a complete remission (CR) within 60 days of initiation of protocol therapy, or relapse, or death from any cause, showed a statistically significant improvement with a median of 8.2 months for RYDAPT plus standard chemotherapy versus 3.0 months for placebo plus standard chemotherapy with HR 0.78 (95% CI 0.66, 0.93) and 2-sided p = 0.005. In an exploratory analysis of EFS defined as a failure to obtain a CR any time during induction, or relapse, or death from any cause with failures assigned as an event on study Day 1, the median EFS was 10.6 months for RYDAPT plus standard chemotherapy versus 5.6 months for placebo plus standard chemotherapy with HR 0.72 (95% CI 0.61, 0.86).

14.2 Systemic Mastocytosis

Study 2

A single-arm, open-label, multicenter trial evaluated the efficacy of RYDAPT as a single agent in ASM, SM-AHN, and MCL, collectively referred to as advanced SM. The study enrolled 116 adult patients with relapse or progression to 0, 1, or 2 prior regimens for SM. The study excluded patients with serum creatinine > 2.0 mg/dL, hepatic transaminases > 2.5 x ULN or > 5 x ULN if disease-related, total bilirubin > 1.5 x ULN or > 3 x ULN if disease-related, QTc > 450 msec, cardiovascular disease, including left-ventricular ejection fraction < 50%, or any pulmonary infiltrates. In addition, the study excluded patients with acute-stage or life-threatening AHN. Patients received RYDAPT 100 mg orally twice daily in 28-day cycles until disease progression or intolerable toxicity.

Of the 116 patients treated, a study steering committee identified 89 patients who had measurable C-findings and were evaluable for response. The median age in this group was 64 years (range, 25 to 82), 64% of patients were male, and nearly all patients (97%) were Caucasian. Among these patients, 36% had prior therapy for SM, and 82% had the KIT D816V mutation detected at baseline. Their median duration of treatment was 11 months (range, < 1 to 68 months), with treatment ongoing in 17%.

Efficacy was established on the basis of confirmed complete remission (CR) plus incomplete remission (ICR) by 6 cycles of RYDAPT by modified Valent criteria for ASM and SM-AHN (Table 7). Table 7 shows responses to RYDAPT according to modified Valent criteria. Confirmed major or partial responses occurred in 46 of 73 patients with a documented KIT D816V mutation, 7 of 16 with wild-type or unknown status with respect to KIT D816V mutation, and 21 of 32 having prior therapy for SM.

Table 7: Efficacy of RYDAPT in Systemic Mastocytosis per Modified Valent Criteria (Study 2)
Modified Valent Criteria | All Patients Evaluatede (N = 89) | ASM (N = 16) | SM-AHN (N = 57) | MCL (N = 16)
CR + ICR by 6 cycles, na,b (95% CI, %) | 19 (21%) (13, 31) | 6 (38%) (15, 65) | 9 (16%) (7, 28) | 4 (25%) (7, 52)
Median duration of CR + ICR (months)c (95% CI) Ranged | NR (24.1, NE) 6.6+, 65.8+ | NR (24.1, NE) 12.1+, 36.8+ | NR (7.4, NE) 6.6+, 52.1+ | NR (NE, NE) 19.1+, 65.8+
Median time to CR + ICR (months) Range | 0.5 0.1, 3.0 | 0.7 0.3, 1.9 | 0.5 0.1, 3.0 | 0.3 0.1, 0.5
Abbreviations: ASM, aggressive systemic mastocytosis; CI, confidence interval; CR, complete remission; ICR, incomplete remission; MCL, mast cell leukemia; NE, not estimated; NR, not reached; SM-AHN, systemic mastocytosis with associated hematological neoplasm.
aPer Study Steering Committee. Response confirmation after ≥ 8 weeks was required. No CRs were reported.
bPatients who received concomitant high-dose corticosteroids were considered unevaluable and were excluded from response assessment.
cAmong patients with a response of CR or ICR. The estimated median follow-up for duration of response (DOR) was 35.4 months overall.
dA "+" sign indicates a censored value.
e25 patients were not assessable for the presence of MCL on central histopathology review, and 11 patients with unconfirmed presence of AHN were regarded as not having AHN.

As a post-hoc exploratory analysis, efficacy was also assessed using modified 2013 International Working Group-Myeloproliferative Neoplasms Research and Treatment-European Competence Network on Mastocytosis (IWG-MRT-ECNM) consensus criteria. Response after 6 cycles of RYDAPT was determined using a computational algorithm. The efficacy of RYDAPT for MCL was based on the CR results by these criteria. There were 115 patients evaluable for response assessment, of whom 47 (41%) had prior therapy for SM, and 93 (81%) had a documented D816V mutation at baseline. Table 8 provides the results of this analysis. Overall response by modified IWG-MRT-ECNM criteria was reported for 16 (17%) of 93 patients with a documented D816V mutation, and in 8 (17%) of 47 patients having prior therapy for SM.

Table 8: Efficacy of RYDAPT in Systemic Mastocytosis per Modified IWG-MRT-ECNM Consensus Criteria Using an Algorithmic Approach (Study 2)
 | All Patients Evaluated (N = 115)b,c | ASM (N = 16) | SM-AHN (N = 72) | MCL (N = 21) | Subtype not Established (N = 6)
Overall response in 6 cycles, na (95% CI) | 19 (17%) (10, 25) | 5 (31%) (11, 59) | 8 (11%) (5, 21) | 4 (19%) (5, 42) | 2 (33%) (4, 78)
Best overall response, n Complete remission Partial remission | 2 (2%) 17 (15%) | 1 (6%) 4 (25%) | 0 (0%) 8 (11%) | 1 (5%) 3 (14%) | 0 (0%) 2 (33%)
Duration of response (months)d Rangee | 6.8+, 60.5+ | 10.2+, 36.4+ | 6.8+, 51.8+ | 8.6+, 55.9+ | 27.3+, 60.5+
Abbreviations: ASM, aggressive systemic mastocytosis; IWG-MRT-ECNM, international working group-myeloproliferative neoplasms research and treatment-european competence network on mastocytosis; MCL, mast cell leukemia; SM-AHN, systemic mastocytosis with associated hematological neoplasm.
aDetermined with 12-week confirmation. Patients who received high-dose corticosteroids were considered evaluable for response.
bMedian exposure to midostaurin was 11.5 (range, 0.3, 68.3) months.
c31 patients were not assessable for MCL on central review, and 15 patients with unconfirmed AHN were classified as not having AHN.
dMedian duration of response (DOR) was not reached in any subtype. Median follow up for DOR, among all responders, was 35.0 months.
eA “+” sign indicates a censored value.

Study 3

Study 3 was a single-arm, multicenter, open-label trial of 26 patients with advanced SM. RYDAPT was administered orally at 100 mg twice daily with food. The median age in this group was 64 years, 58% of patients were male and most were Caucasian (81%). Eligibility criteria were similar to Study 2. By Valent criteria per investigator assessment, of 17 patients with SM-AHN, 10 achieved a response (1 partial, 9 major) by 2 cycles that was sustained for at least 8 weeks. Patients who received concomitant corticosteroids were included. Of the 6 patients with MCL, 1 achieved partial response and 1 achieved major response. Median duration of response (DOR) for either group had not been reached, with DOR ranging from 3.4+ to 79.2+ months in patients with SM-AHN and 28.6+ to 32.1+ months in patients with MCL. The subtype of SM in the remaining 3 patients was unconfirmed.

16 HOW SUPPLIED/STORAGE AND HANDLING

RYDAPT 25 mg capsules

Pale orange oblong soft capsule with red ink imprint ‘PKC NVR’; available in:

56 soft capsules………………………………………………………………………………………NDC 0078-0698-99

Contents: Each carton contains two inner packs, each with 28 capsules (7 blister cards with 4 capsules each)

112 soft capsules……………………………………………………………………………………..NDC 0078-0698-19

Contents: Each carton contains four inner packs, each with 28 capsules (7 blister cards with 4 capsules each)

Store at 20°C to 25°C (68°F to 77°F); excursions permitted between 15°C and 30°C (59°F and 86°F) [see USP Controlled Room Temperature]. Store in the original container to protect from moisture.

17 PATIENT COUNSELING INFORMATION

Advise the patient to read the FDA-approved patient labeling (Patient Information).

Pulmonary Adverse Reactions

Inform patients to seek medical attention for new cough, chest discomfort, or shortness of breath [see Warnings and Precautions (5.2)].

Gastrointestinal Adverse Reactions

Inform patients that RYDAPT can cause nausea, vomiting, and diarrhea. Advise patients to contact their healthcare provider if these symptoms occur or are persisting despite supportive medications [see Adverse Reactions (6.1)].

Embryo-Fetal Toxicity

- Advise pregnant women and females of reproductive potential of the potential risk to a fetus. Advise females of reproductive potential to use effective contraception during treatment with RYDAPT and for 4 months after the last dose. Advise females to inform their healthcare provider of a known or suspected pregnancy [see Warnings and Precautions (5.1), Use in Specific Populations (8.1, 8.3)].
- Advise male patients with female partners of reproductive potential to use effective contraception during treatment with RYDAPT and for 4 months after the last dose [see Use in Specific Populations (8.3)].
- Advise females who may have been exposed to RYDAPT during pregnancy directly or through male partner receiving RYDAPT therapy to contact the Novartis Pharmaceuticals Corporation at 1-888-669-6682 and/or at https://report.novartis.com/ [see Use in Specific Populations (8.1)].

Lactation

Advise women not to breastfeed during treatment with RYDAPT and for 4 months after the last dose [see Use in Specific Populations (8.2)].

Infertility

Advise females and males of reproductive potential that RYDAPT may impair fertility [see Use in Specific Populations (8.3), Nonclinical Toxicology (13.1)].

Distributed by:
Novartis Pharmaceuticals Corporation
One Health Plaza
East Hanover, New Jersey 07936

T2023-25

PATIENT INFORMATION
RYDAPT® (rye-dapt)
(midostaurin)
capsules

What is RYDAPT?
RYDAPT is a prescription medicine used to treat adults:

- newly diagnosed with a certain type of acute myeloid leukemia (AML), in combination with certain chemotherapy medicines
  - Your healthcare provider will perform a test to make sure RYDAPT is right for you.
- with aggressive systemic mastocytosis (ASM), systemic mastocytosis with associated hematological neoplasm (SM-AHN), or mast cell leukemia (MCL)

RYDAPT is not safe when given to children in combination with chemotherapy. It is not known if RYDAPT is effective in children.

Do not take RYDAPT if you are allergic to midostaurin or any of the ingredients in RYDAPT. See the end of this leaflet for a complete list of ingredients in RYDAPT.

- Signs and symptoms of an allergic reaction to RYDAPT have included trouble breathing, flushing, chest pain, throat tightness, and swelling of your lips, mouth, or throat. Get medical help right away if you have any of these signs or symptoms.

Before you take RYDAPT, tell your healthcare provider about all of your medical conditions, including if you:

- have any lung or breathing problems
- are pregnant or plan to become pregnant. RYDAPT may cause harm to your unborn baby. Tell your healthcare provider right away if you become pregnant during treatment with RYDAPT or think you may be pregnant. Pregnancy Registry: There is a pregnancy registry that monitors the health of females and their babies exposed to RYDAPT during pregnancy. Females who have taken RYDAPT during pregnancy or have been exposed to RYDAPT during pregnancy through a male partner taking RYDAPT should contact Novartis Pharmaceuticals Corporation at 1-888-669-6682, or at https://report.novartis.com/.
  - If you are able to become pregnant, your healthcare provider may perform a pregnancy test within 7 days before you start RYDAPT.
  - Females who are able to become pregnant should use effective birth control (contraception) during treatment with RYDAPT and for 4 months after the last dose of RYDAPT.
  - Males who have female partners that are able to become pregnant should use effective birth control during treatment with RYDAPT and for 4 months after the last dose of RYDAPT.
- are breastfeeding or plan to breastfeed. It is not known if RYDAPT passes into your breast milk. You should not breastfeed during treatment with RYDAPT and for 4 months after the last dose of RYDAPT.

Tell your healthcare provider about all the medicines you take, including prescription and over-the-counter medicines, vitamins, and herbal supplements.

How should I take RYDAPT?

- Take RYDAPT exactly as your healthcare provider tells you.
- Your healthcare provider will tell you how many capsules of RYDAPT you need to take. Do not change your dose unless your healthcare provider tells you to.
- Your healthcare provider will prescribe medicines to help prevent the nausea and vomiting during treatment with RYDAPT.
- Take RYDAPT 2 times a day (about every 12 hours apart).
- Take RYDAPT with food.
- Do not open or crush RYDAPT capsules.
- If you miss a dose of RYDAPT, take your next dose at your scheduled time. Do not take an extra dose to make up for a missed dose.
- If you vomit after taking a dose of RYDAPT, do not take an extra dose. Take your next dose at your scheduled time.

What are the possible side effects of RYDAPT?
RYDAPT may cause serious side effects, including:

- Lung problems. RYDAPT may cause lung problems that may lead to death when used alone or in combination with other chemotherapy medicines. Get medical help right away if you have any new or worsening lung symptoms, including cough, chest discomfort, or shortness of breath.

The most common side effects of RYDAPT in people with AML include:

- low white blood cell counts with fever (febrile neutropenia)
- nausea
- redness, pain, or ulcers on the inside your mouth (mucositis)
- vomiting
- headache
- bruising

- muscle or bone pain
- nose bleeds
- device-related infection
- high blood sugar levels (hyperglycemia)
- upper respiratory tract infection
- abnormal electrocardiogram (QT prolongation)

The most common side effects of RYDAPT in people with ASM, SM-AHN, or MCL include:

- nausea
- vomiting
- diarrhea
- swelling in your hands, feet, or ankles
- muscle or bone pain
- stomach-area pain

- tiredness
- upper respiratory tract infection
- constipation
- fever
- headache
- trouble breathing

Call or inform your healthcare provider if nausea, vomiting or diarrhea occurs, gets worse or does not go away.
RYDAPT may cause fertility problems in females and males, which may affect your ability to have children. Talk to your healthcare provider if you have concerns about fertility.
Your healthcare provider may tell you to decrease your dose, temporarily stop, or completely stop taking RYDAPT if you develop certain side effects during treatment with RYDAPT.
Your healthcare provider will do blood tests to check you for side effects during treatment with RYDAPT.
These are not all of the possible side effects of RYDAPT. Call your doctor for medical advice about side effects. You may report side effects to FDA at 1-800-FDA-1088.

How should I store RYDAPT?

- Store RYDAPT at room temperature at 68°F to 77°F (20°C to 25°C).
- Keep RYDAPT in the original container to protect from moisture.

Keep RYDAPT and all medicines out of the reach of children.

General information about the safe and effective use of RYDAPT.
Medicines are sometimes prescribed for conditions not listed in the Patient Information leaflet. Do not take RYDAPT for a condition for which it was not prescribed. Do not give RYDAPT to other people, even if they have the same condition or symptoms you have. It may harm them. You can ask your pharmacist or healthcare provider for information about RYDAPT that is written for healthcare professionals.

What are the ingredients in RYDAPT?
Active ingredient: midostaurin
Inactive ingredients: carmine, corn oil mono-di-triglycerides, dehydrated alcohol, ferric oxide red, ferric oxide yellow, gelatin, glycerin 85%, hypromellose 2910, polyethylene glycol 400, polyoxyl 40 hydrogenated castor oil, propylene glycol, purified water, titanium dioxide, and vitamin E.

Distributed by: Novartis Pharmaceuticals Corporation, One Health Plaza, East Hanover, New Jersey 07936

© Novartis

For more information about RYDAPT, visit www.US.RYDAPT.com.

This Patient Information has been approved by the U.S. Food and Drug Administration.

Revised: November 2021

T2021-150

PRINCIPAL DISPLAY PANEL

Rydapt®

NDC 0078-0698-99

(midostaurin)
Capsules

25 mg

Rx only

56 soft capsules

Contents: 2 packs containing 28 capsules each

NOVARTIS